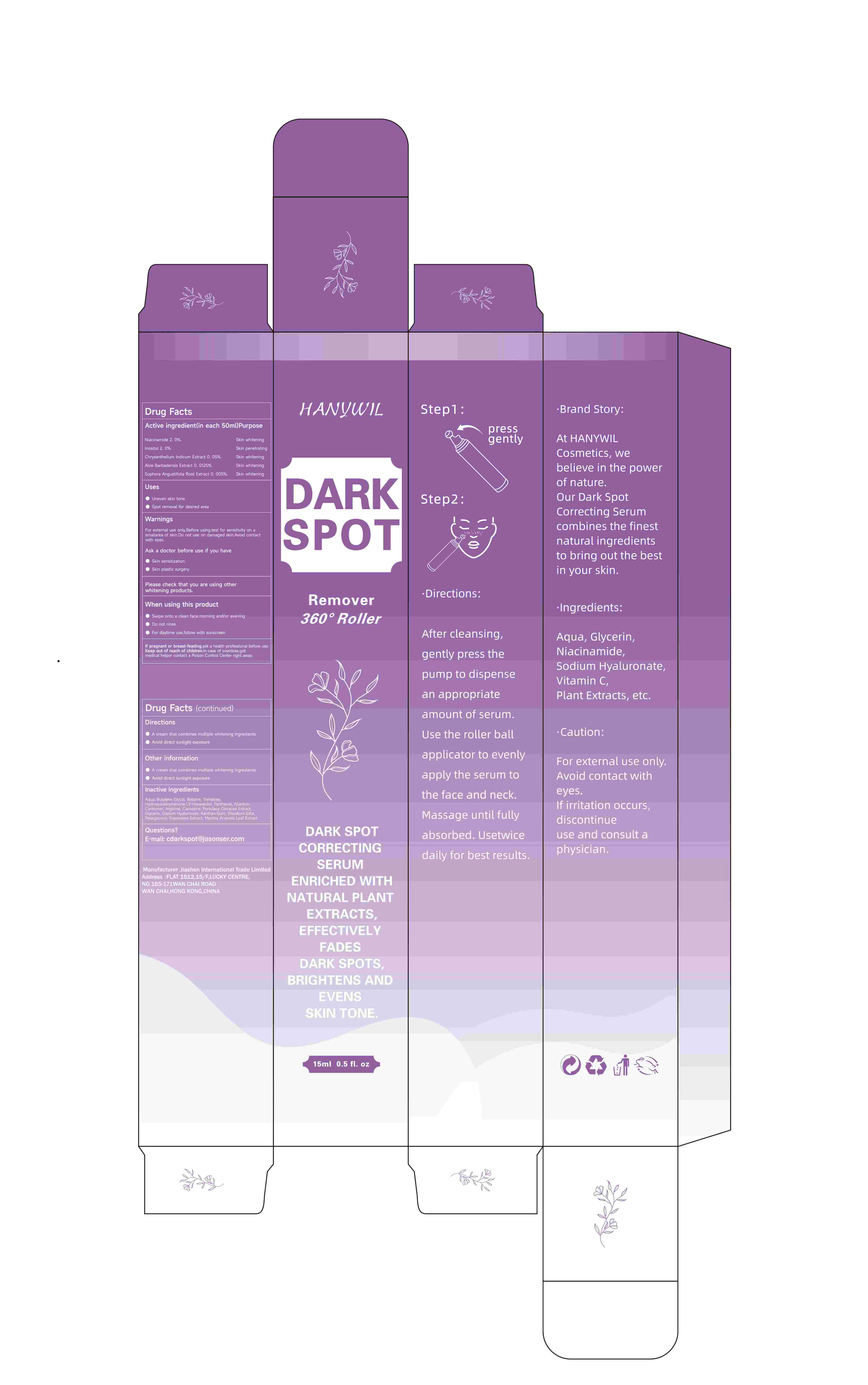 DRUG LABEL: HANYWIL DARK SPOT
NDC: 84867-004 | Form: SOLUTION, GEL FORMING / DROPS
Manufacturer: Jiashen International Trade Limited
Category: otc | Type: HUMAN OTC DRUG LABEL
Date: 20241122

ACTIVE INGREDIENTS: NIACINAMIDE 2000 mg/50 mL; ALOE BARBADENSIS FLOWER EXTRACT 125 mg/50 mL; SOPHORA FLAVESCENS ROOT 5 mg/50 mL; INOSITOL 1500 mg/50 mL; CHRYSANTHELLUM INDICUM TOP 50 mg/50 mL
INACTIVE INGREDIENTS: PORTULACA OLERACEA LEAF; MENTHA ARVENSIS LEAF; 1,2-HEXANEDIOL; HYDROXYACETOPHENONE; DIMETHICONE 350; FRAGRANCE 13576; SQUALANE; EDETATE DISODIUM; ETHYLHEXYLGLYCERIN; ALPHA-TOCOPHEROL ACETATE; CARBOMER; GLYCERIN; CETEARYL GLUCOSIDE; GLYCERYL STEARATE/PEG-100 STEARATE; PHENOXYETHANOL; ALOE BARBADENSIS LEAF EXTRACT; HAMAMELIS VIRGINIANA TOP WATER; CAPRYLIC/CAPRIC TRIGLYCERIDE; PELARGONIUM GRAVEOLENS LEAF OIL; CETEARYL ALCOHOL; BUTYROSPERMUM PARKII (SHEA) BUTTER; PROPYLENE GLYCOL

ACTIVE INGREDIENT

NIACINAMIDE
INOSITOL
Chrysanthellum Indicum Extract
Aloe Barbadensis Extract
Sophora Angustifolia Root Extract

INACTIVE INGREDIENT

WATER
GLYCERIN
PROPYLENE GLYCOL
CAPRYLIC/CAPRIC TRIGLYCERIDE
CETEARYL ALCOHOL
CETEARYL GLUCOSIDE
DIMETHICONE
BUTYROSPERMUM PARKII (SHEA) BUTTER
GLYCERYL STEARATE
PORTULACA OLERACEA EXTRAC
CHRYSANTHELLUM INDICUM EXTRACT
PELARGONIUM GRAVEOLENS EXTRACT
MENTHA ARVENSIS LEAF EXTRACT
ALOE BARBADENSIS EXTRACT
SOPHORA ANGUSTIFOLIA ROOT EXTRACT
SQUALANE
TOCOPHERYL ACETATE
1,2-HEXANEDIOL
HYDROXYACETOPHENONE
PHENOXYETHANOL
ETHYLHEXYLGLYCERIN
CARBOMER
DISODIUM EDTA
FRAGRANCE

PURPOSE

DARK SPOTCORRECTINGSERUMENRICHED WITHNATURAL PLANTEXTRACTS,EFFECTIVELYFADESDARK SPOTSBRIGHTENS ANDEVENSSKIN TONE.

Ask a doctor before use if you have
WarningsFor extemmal use only,. Before using,test forsensitivity on a smallarea of skin. Do not use ondamaged skin. Avoid contact with eves
Skin sensitization.
Skin plastic surgery

STOP USE

If pregnant or breast-feading, ask a health
professional before use. Keep out of reach of
children. In case of overdose,got medical help
or contact a Poison Control Center right away.

For external use only. Before using,test for
sensitivity on a small area of skin. Do not use on
damaged skin. Avoid contact with eyes.

Keep out of reach of
children. In case of overdose,got medical help
or contact a Poison Control Center right away.

Directions:
After cleansing,gentty press thepump to dispensean appropriate
amount of serum.
Use the roller ball
applicator to evenly
appty the serum tothe face and neck.Massage until fullyabsorbed.Usetwicedaily for best results

Directions:
After cleansing,gentty press thepump to dispensean appropriate
amount of serum.
Use the roller ball
applicator to evenly
appty the serum tothe face and neck.Massage until fullyabsorbed.Usetwicedaily for best results

DOSAGE AND ADMINISTRATION

Step 2: Take an appropriateamount of dark spotcream and applyevenly to the desiredarea, massage gentlyfor 1-2 minutes.Step 3: Use twice aday, with massage tohelp absorption,adhere to the use ofmore than a month thebest results.